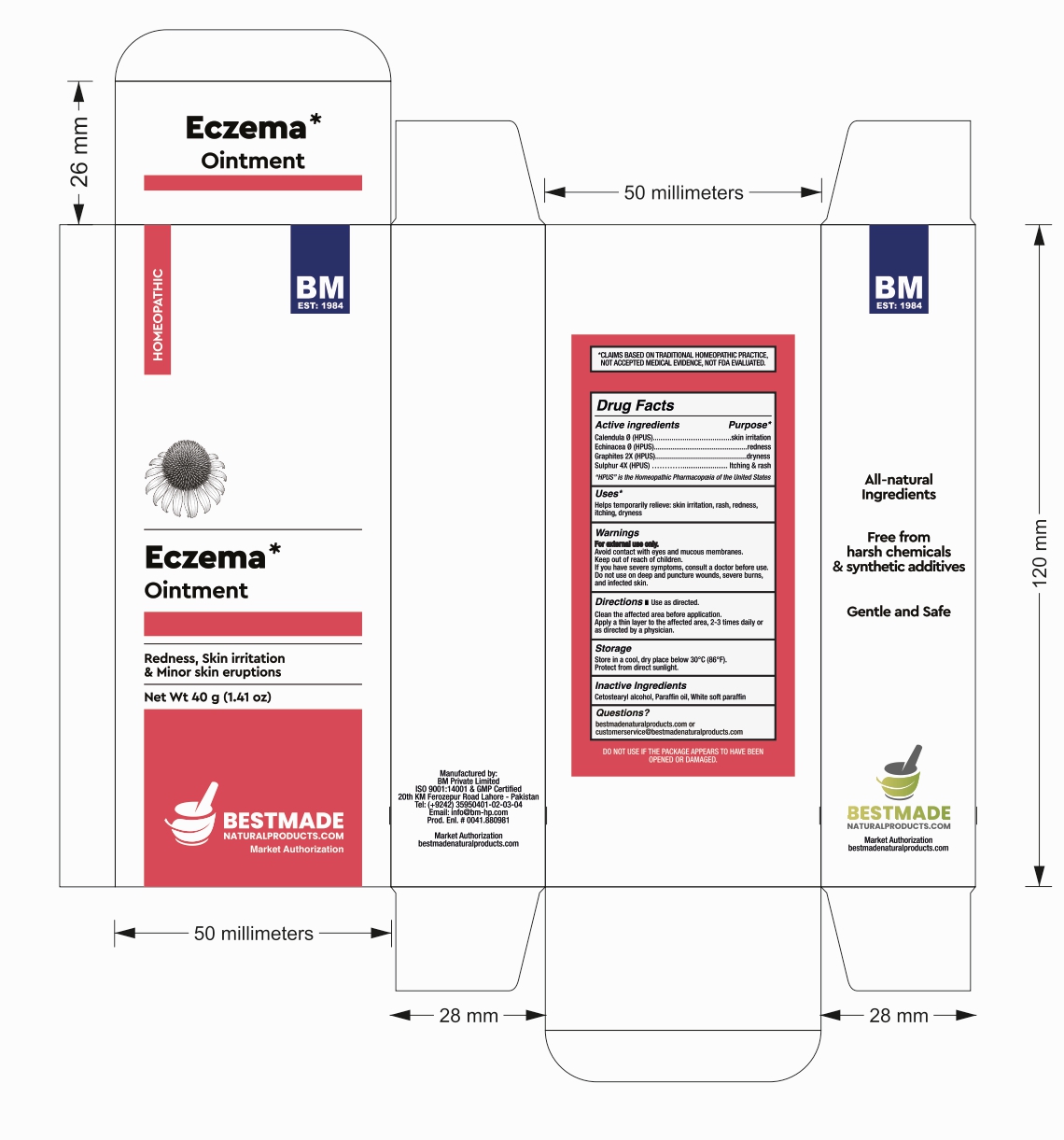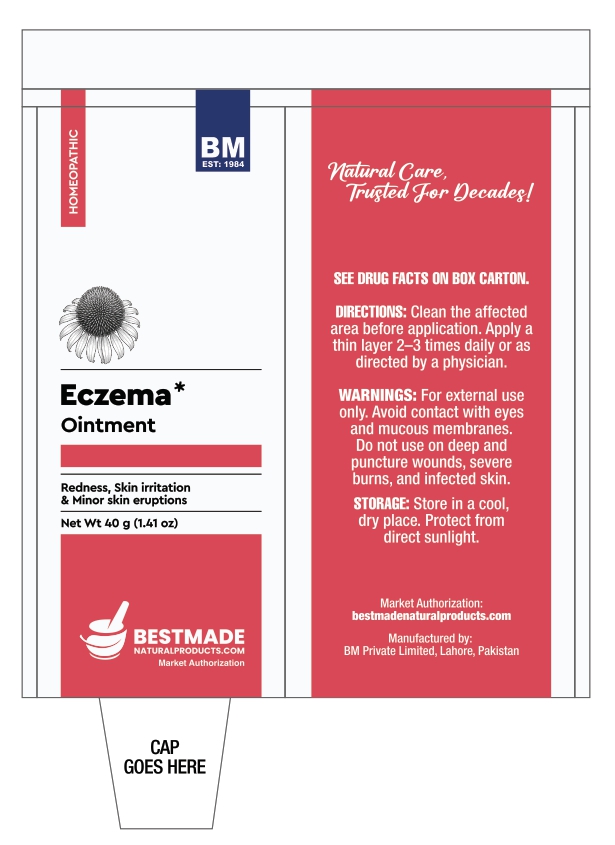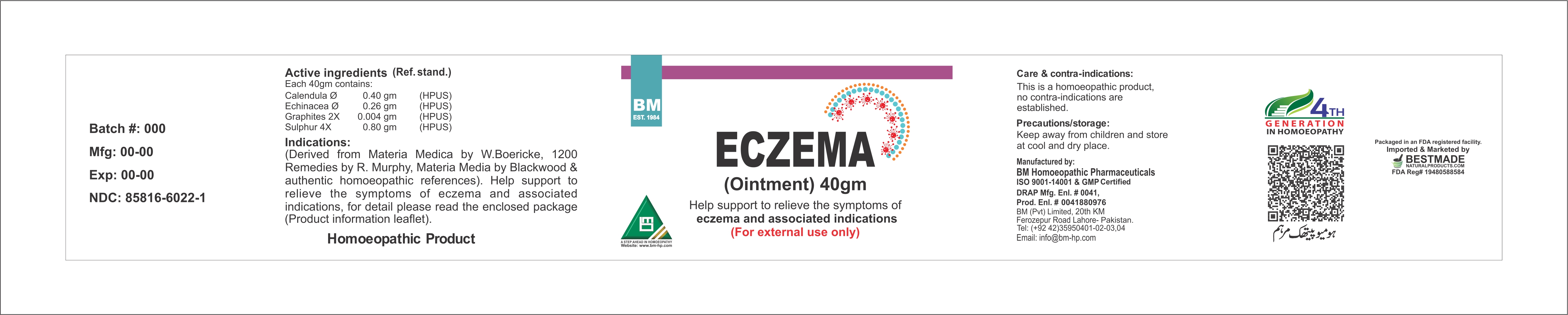 DRUG LABEL: BM Eczema
NDC: 85816-6022 | Form: OINTMENT
Manufacturer: BM Private Limited
Category: homeopathic | Type: HUMAN OTC DRUG LABEL
Date: 20260212

ACTIVE INGREDIENTS: ECHINACEA, UNSPECIFIED 1 [hp_X]/1 g; GRAPHITE 2 [hp_X]/1 g; CALENDULA OFFICINALIS FLOWERING TOP 1 [hp_X]/1 g; SULFUR 4 [hp_X]/1 g
INACTIVE INGREDIENTS: CETOSTEARYL ALCOHOL 0.095 g/1 g; WHITE PETROLATUM 0.865 g/1 g; MINERAL OIL 0.04 g/1 g

BM Eczema Ointment

ACTIVE INGREDIENT

Active ingredients (Ref. stand.) Each 40gm contains: Calendula ∅ (HPUS) Echinacea ∅ (HPUS) Graphites 2X (HPUS) Sulphur 4X (HPUS)

INACTIVE INGREDIENT

CETOSTEARYL ALCOHOL, PARAFFIN OIL, WHITE SOFT PARAFFIN

Uses*

Helps temporarily relieve: skin irritation, rash, redness, itching, dryness

Active ingredients Purpose*

Calendula Ø (HPUS)..................skin irritation

Echinacea Ø (HPUS).................redness

Graphites 2X (HPUS).............dryness

Sulphur 4X (HPUS) …………. Itching & rash

Warnings:

For external use only.

Avoid contact with eyes and mucous membranes.

Keep out of reach of children.

If you have severe symptoms, consult a doctor before use.

Do not use on deep and puncture wounds, severe burns, and infected skin.

Warnings:

Keep out of reach of children.

Storage:

Store in a cool, dry place below 30°C (86°F).

Protect from direct sunlight.

Directions:

Use as directed.

Clean the affected area before application.

Apply a thin layer to the affected area, 2-3 times daily or as directed by a physician.

Package 1:

Package 2: Tube

Carton Box